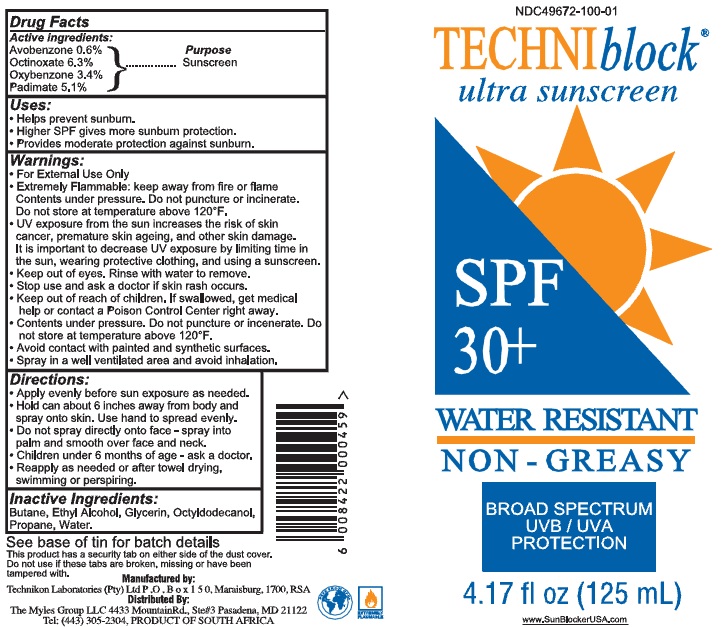 DRUG LABEL: TECHNIblock ULTRA SUNSCREEN
NDC: 49672-100 | Form: LOTION
Manufacturer: The Myles Group LLC
Category: otc | Type: HUMAN OTC DRUG LABEL
Date: 20100929

ACTIVE INGREDIENTS: AVOBENZONE 0.6 mL/100 mL; OCTINOXATE 6.3 mL/100 mL; OXYBENZONE 3.4 mL/100 mL; PADIMATE A 5.1 mL/100 mL
INACTIVE INGREDIENTS: BUTANE; ALCOHOL; GLYCERIN; OCTYLDODECANOL; PROPANE; WATER

TECHNIblock ULTRA SUNSCREEN

Drug Facts:

Active Ingredients: Purpose

Avobenzone 0.5% Sunscreen

Octinoxate 6.3% Sunscreen

Oxybenzone 3.4% Sunscreen

Padimate 5.1% Sunscreen

Uses:

Helps prevent Sunburn

Higher SPF gives more sunburn protection.

Provides moderate protection against sunburn.

Warnings:
• For External Use Only
• Extremely Flammable: keep away from fire or flame
Contents under pressure. Do not puncture or incinerate.
Do not store at temperature above 120°F.
• UV exposure from the sun increases the risk of skin cancer,
premature skin ageing, and other skin damage. It is important
to decrease UV exposure by limiting time in the sun, wearing
protective clothing, and using a sunscreen.
• Keep out of eyes. Rinse with water to remove.

-Stop use and ask a doctor if skin rash occurs

-Keep out of reach of children. If swallowed, get medical help or contact a Poison Control Center right away.

• Contents under pressure. Do not puncture or incenerate. Do not store at temperatures above 120F
• Avoid contact with painted and synthetic surfaces.
• Spray in a well ventilated area and avoid inhalation.

WHEN USING

Keep out of eyes. Rinse with water
to remove.

Stop use and ask a doctor if skin rash occurs.

Stop use and ask a doctor if skin rash occurs.

Keep out of reach of children. If swallowed, get medical
help or contact a Poison Control Center right away.

STORAGE AND HANDLING

Contents under pressure. Do not puncture or incenerate. Do
not store at temperature above 120°F.

DOSAGE AND ADMINISTRATION

• Apply evenly before sun exposure as needed.

• Hold can about 6 inches away from body and spray onto
skin. Use hand to spread evenly.
• Do not spray directly onto face - spray into palm and
smooth over face and neck.
• Children under 6 months of age - ask a doctor.
• Reapply as needed or after towel drying, swimming or
perspiring.

INACTIVE INGREDIENT

Butane, Ethyl Alcohol, Glycerin, Octyldodecanol, Propane,
Water.

DESCRIPTION

See base of tin for batch details
This product has a security tab on either side of the
dust cover. Do not use if these tabs are broken,
missing or have been tampered with.

Manufactured by:
Technikon Laboratories (Ply) Ltd P .0 . Box 1 5 0, Maraisburg, 1700, RSA

Distributed By:
The Myles Group LLC 4433 MountainRd , Ste#3 Pasadena, MD 21122
Tel: (443) 305-2304, PRODUCT OF SOUTH AFRICA

PACKAGE LABEL

NDC49672-100-01

TECHNIblock

ULTRA SUNSCREEN

SPF

30^+

WATER RESISTANT

NON-GREASY

BROAD SPECTRUM

UVB/UVA

PROTECTION

4.17 fl oz

(125 mL)

www.SubBlockerUSA.com